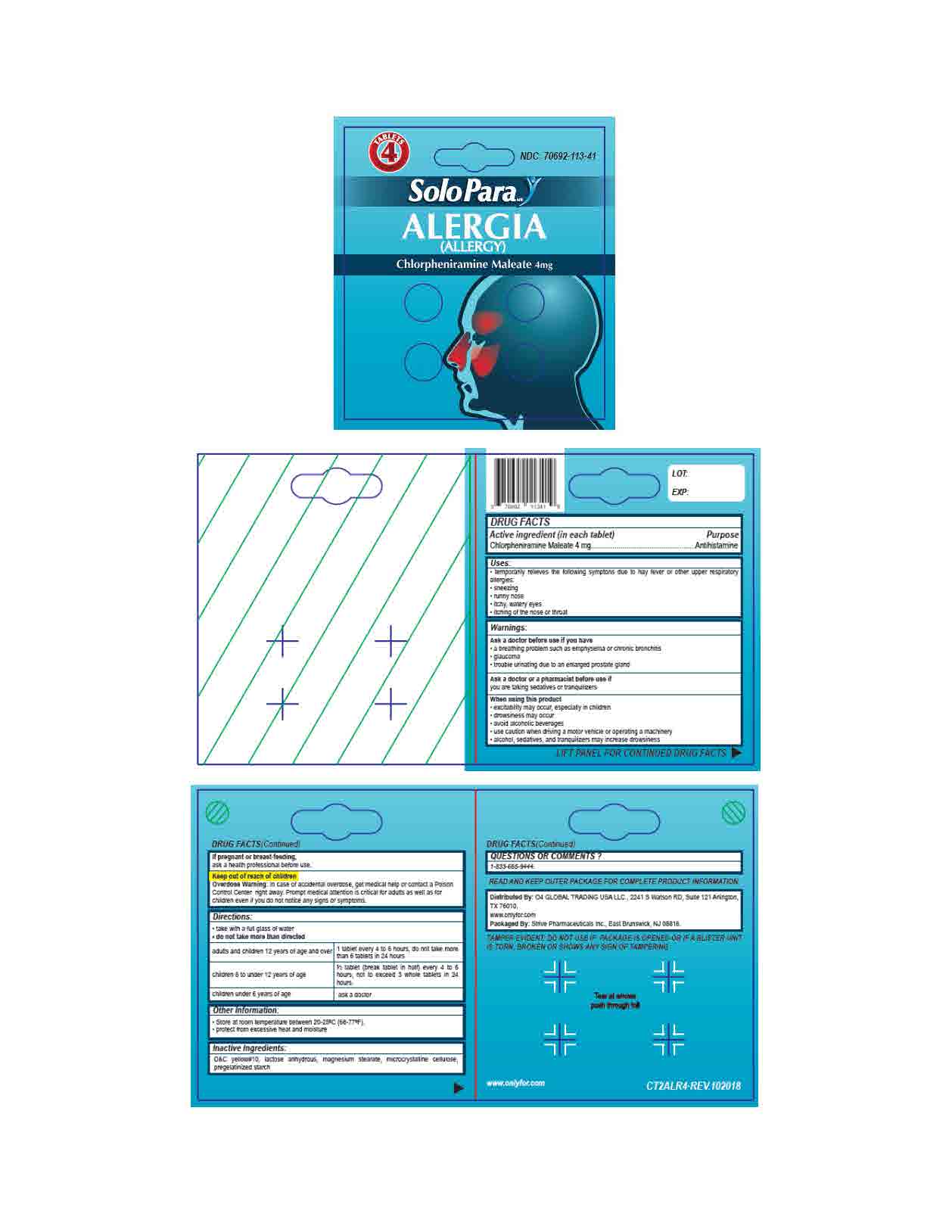 DRUG LABEL: Chlorpheniramine Maleate 4mg
NDC: 70692-113 | Form: TABLET
Manufacturer: Strive Pharmaceuticals Inc
Category: otc | Type: HUMAN OTC DRUG LABEL
Date: 20201116

ACTIVE INGREDIENTS: CHLORPHENIRAMINE MALEATE 4 mg/1 1
INACTIVE INGREDIENTS: CELLULOSE, MICROCRYSTALLINE; STARCH, CORN; LACTOSE MONOHYDRATE; D&C YELLOW NO. 10; MAGNESIUM STEARATE

Allergy - Alergia (Chlorpheniramine Maleate 4mg)

ACTIVE INGREDIENT

Chlorpheniramine Maleate 4mg

INACTIVE INGREDIENT

D&C yellow #10, lactose anhydrous, magnesium stearate, microcrystalline cellulose, pregelatinized starch

DOSAGE AND ADMINISTRATION

- take with a full glass of water
- do not take more than directed

adults and children 12 yers of age and over | 1 tablet every 4 to 6 hours, do not take more than 6 tablets in 24 hours
children 6 to under 12 years of age | 1/2 tablet (break tablet in half) every 4 to 6 hours, not to exceed 3 whole tablets in 24 hours
children under 6 years of age | ask a doctor

INDICATIONS AND USAGE

temporarily relieves the following symptoms due to hay fever or other upper respiratory allergies

- sneezing
- runny nose
- itchy, watery eyes
- itching of the nose or throat

Ask a doctor before use if you have

- a breathing problem such as emphysema or chronic bronchitis
- glaucoma
- trouble urinating due to an enlarged prostrate gland

Ask a doctor or a pharmacist before use if

you sre taking sedatives or tranquilzers

When using this product

- excitability may occur, especially in children
- drowsiness may occur
- avoid alcoholic beverages
- use caution when driving a motor vehicle or operating a machinery
- alcohol, sedatives, and tranquilizers may increase drowsiness

If pregnant or breast-feeding,

ask a health professional before use

Keep out of reach of children

Overdose warning: In case of accidental overdose, get medical help or contact a Poison Control Center right away. Prompt medical attention is critical for adults as well as for children even if you do not notice any signs or symptoms.

Keep out of reach of children

Overdose Warning: In case of accidental overdose, get medical help or contact a Poison Control Center right away. Prompt medical attention is critical for adults as well as for children even if you do not notice any signs or symptoms.

PURPOSE

Antihistamine

OTHER SAFETY INFORMATION

- store at room temperature between 20ºC - 25ºC (68ºF - 77ºF)
- protect from excessive heat and moisture